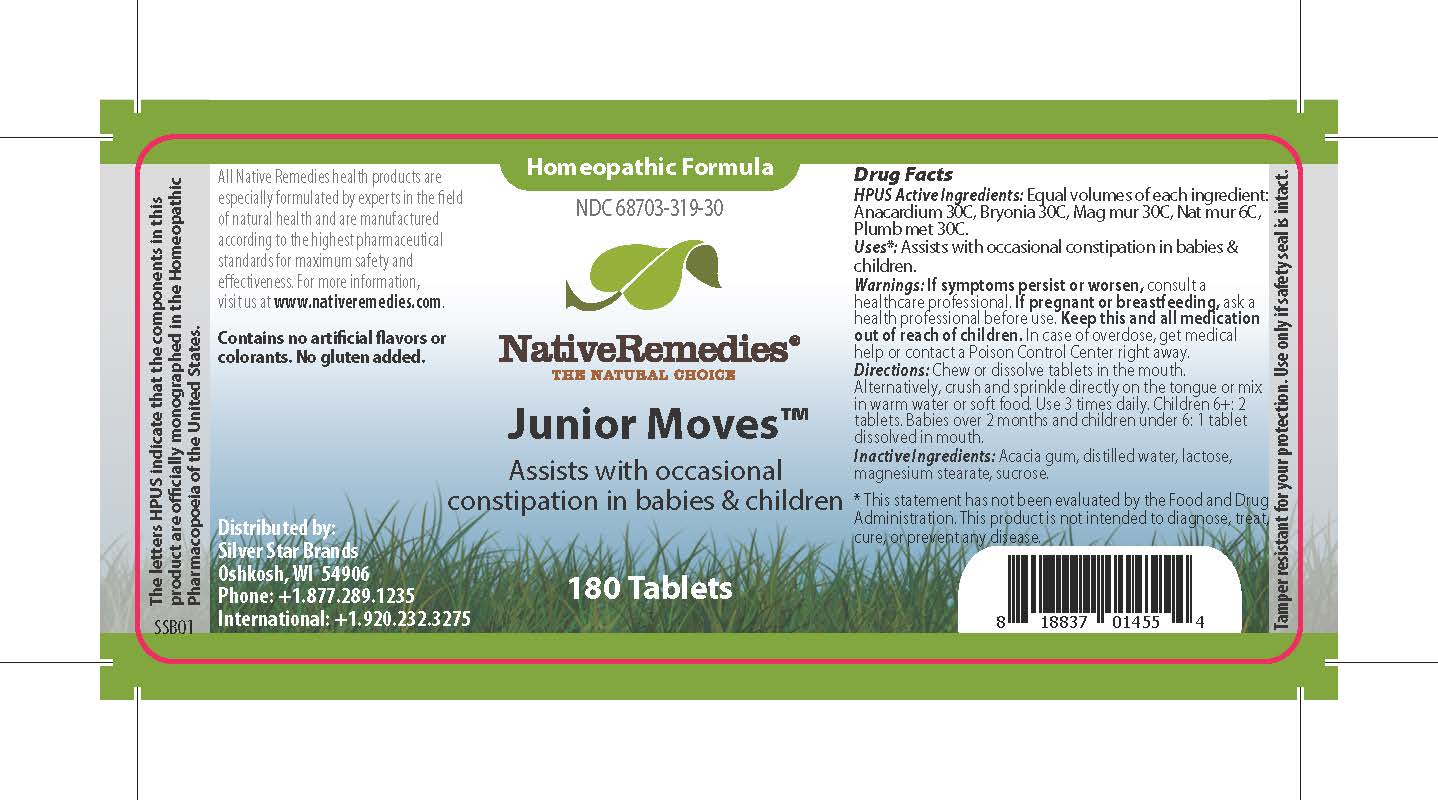 DRUG LABEL: Junior Moves
NDC: 68703-319 | Form: TABLET
Manufacturer: Silver Star Brands
Category: homeopathic | Type: HUMAN OTC DRUG LABEL
Date: 20241203

ACTIVE INGREDIENTS: BRYONIA ALBA ROOT 30 [hp_C]/1 1; MAGNESIUM CHLORIDE 30 [hp_C]/1 1; SODIUM CHLORIDE 6 [hp_C]/1 1; SEMECARPUS ANACARDIUM JUICE 30 [hp_C]/1 1; LEAD 30 [hp_C]/1 1
INACTIVE INGREDIENTS: LACTOSE, UNSPECIFIED FORM; ACACIA; WATER; SUCROSE; MAGNESIUM STEARATE

NativeRemedies® Junior Moves™

HPUS Active Ingredients: Equal volumes of each ingredient: Anacardium, Bryonia, Mag mur, Nat mur, Plumb met.

The letters HPUS indicate that the components in this product are officially monographed in the Homeopathic Pharmacopoeia of the United States.

Uses*

Uses*: Assists with occasional constipation in babies & children.

Warnings

Warnings: If symptoms persist or worsen, consult a healthcare professional. If pregnant or breastfeeding, ask a health professional before use. Keep this and all medication out of reach of children. In case of overdose, get medical help or contact a Poison Control Center right away.

Directions

Directions: Chew or dissolve tablets in the mouth. Alternatively, crush and sprinkle directly on the tongue or mix in warm water or soft food. Use 3 times daily. Children 6+: 2 tablets. Babies over 2 months and children under 6: 1 tablet dissolved in mouth.

OTHER SAFETY INFORMATION

Contains no artificial flavors or colorants. No gluten added.

Tamper resistant for your protection. Use only if safety seal is intact.

Inactive Ingredients

Inactive Ingredients: Acacia gum, distilled water, lactose, magnesium stearate, sucrose.

KEEP OUT OF REACH OF CHILDREN

Keep this and all medication out of reach of children.

PREGNANCY OR BREAST FEEDING

If pregnant or breastfeeding, ask a health professional before use.

PURPOSE

Assists with occasional constipation in babies & children.